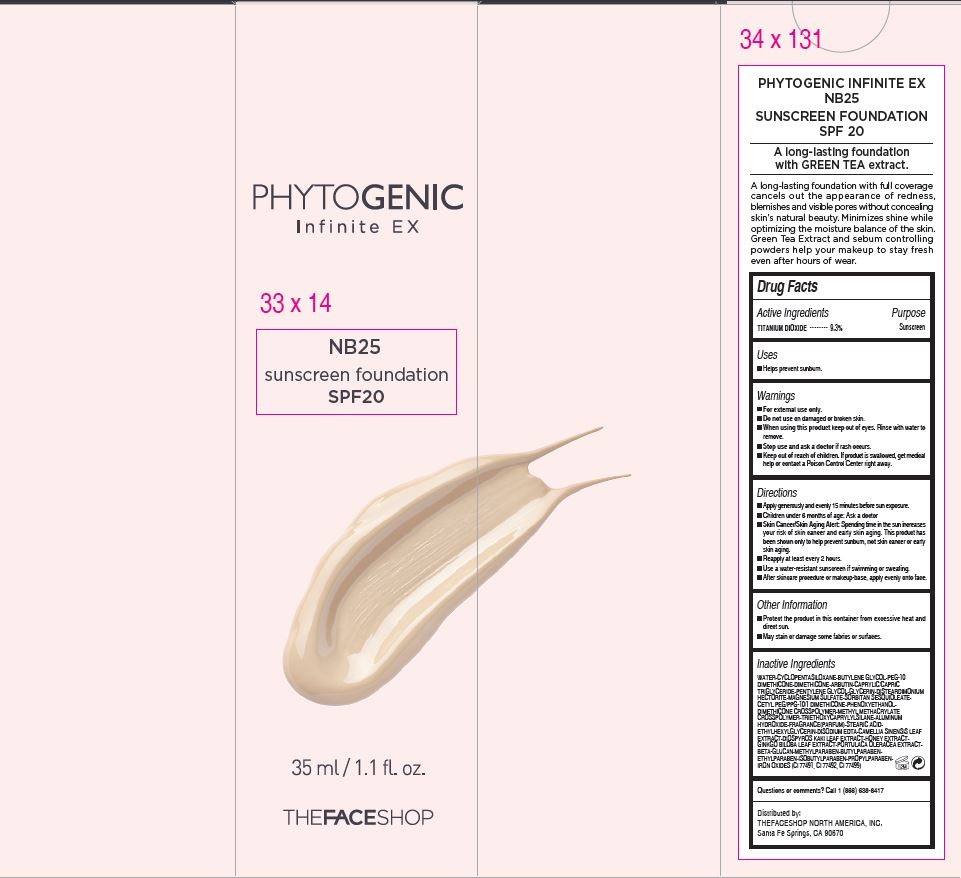 DRUG LABEL: PHYTOGENIC INFINTE EX FOUNDATION
NDC: 51523-455 | Form: CREAM
Manufacturer: THEFACESHOP CO., LTD.
Category: otc | Type: HUMAN OTC DRUG LABEL
Date: 20141120

ACTIVE INGREDIENTS: TITANIUM DIOXIDE 3.26 g/35 mL
INACTIVE INGREDIENTS: WATER

PHYTOGENIC INFINTE EX FOUNDATION 37100455

Active Ingredients

TITANIUM DIOXIDE • • • • • • • • 9.3%

Purpose

Sunscreen

Warnings

For external use only.

Do not use on damaged or broken skin

When using this product keep out of eyes. Rinse with water to remove.

Stop use and ask a doctor if rash occurs.

Keep out of reach of children. If product is swallowed, get medical help or contact a Poison Control Center right away.

Directions

Apply generously and evenly 15 minutes before sun exposure.
Children under 6 months of age: Ask a doctor
Skin Cancer/Skin Aging Alert: Spending time in the sun increases
your risk of skin cancer and early skin aging. This product has
been shown only to help prevent sunburn, not skin cancer or early
skin aging.
Reapply at least every 2 hours.
Use a water-resistant sunscreen if swimming or sweating.
After skincare procedure or makeup-base, apply evenly onto face.

Other Information

Protect the product in this container from excessive heat and
direct sun.
May stain or damage some fabrics or surfaces.

Inactive Ingredients

WATER•CYCLOPENTASILOXANE•BUTYLENE GLYCOL•PEG-10
DIMETHICONE•DIMETHICONE•ARBUTIN•CAPRYLIC/CAPRIC
TRIGLYCERIDE•PENTYLENE GLYCOL•GLYCERIN•DISTEARDIMONIUM
HECTORITE•MAGNESIUM SULFATE•SORBITAN SESQUIOLEATE•
CETYL PEG/PPG-10/1 DIMETHICONE•PHENOXYETHANOL•
DIMETHICONE CROSSPOLYMER•METHYL METHACRYLATE
CROSSPOLYMER•TRIETHOXYCAPRYLYLSILANE•ALUMINUM
HYDROXIDE•FRAGRANCE(PARFUM)•STEARIC ACID•
ETHYLHEXYLGLYCERIN•DISODIUM EDTA•CAMELLIA SINENSIS LEAF
EXTRACT•DIOSPYROS KAKI LEAF EXTRACT•HONEY EXTRACT•
GINKGO BILOBA LEAF EXTRACT•PORTULACA OLERACEA EXTRACT•
BETA-GLUCAN•METHYLPARABEN•BUTYLPARABEN•
ETHYLPARABEN•ISOBUTYLPARABEN•PROPYLPARABEN•
IRON OXIDES (CI 77491, CI 77492, CI 77499)

Questions or comments? Call 1 (866) 638-8417

Distributed by:

THEFACESHOP NORTH AMERICA, INC.
Santa Fe Springs, CA 90670

PACKAGE LABEL

PHYTOGENIC INFINITE EX
NB25
SUNSCREEN FOUNDATION
SPF 20

A long-lasting foundation
with GREEN TEA extract.